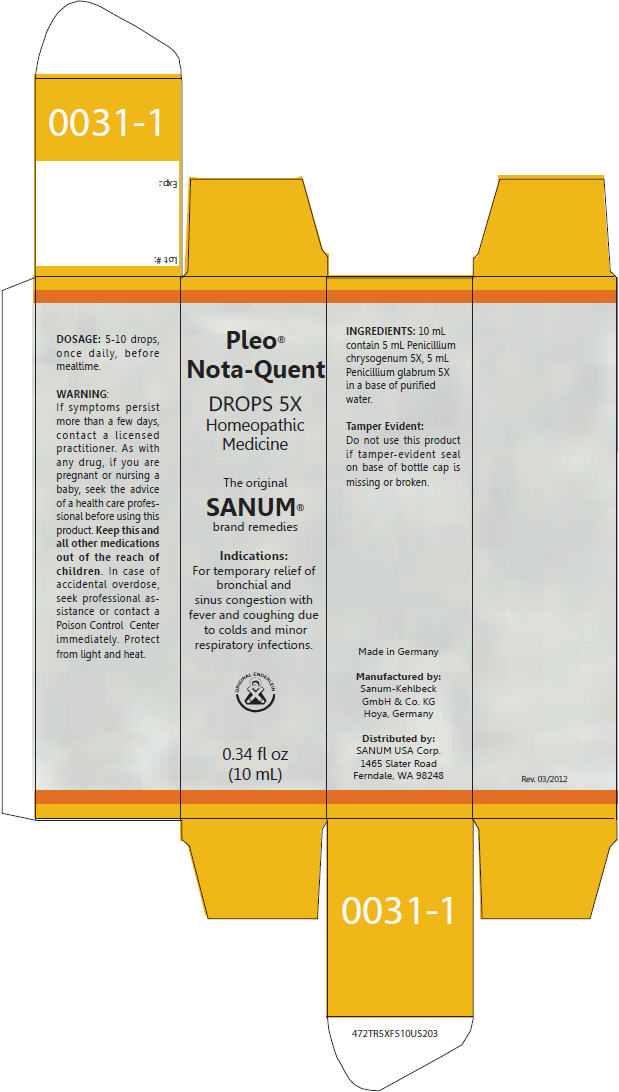 DRUG LABEL: Pleo Nota-Quent
NDC: 60681-0031 | Form: LIQUID
Manufacturer: Sanum-Kehlbeck GmbH & Co. KG
Category: homeopathic | Type: HUMAN OTC DRUG LABEL
Date: 20120413

ACTIVE INGREDIENTS: PENICILLIUM CHRYSOGENUM VAR. CHRYSOGENUM 5 [hp_X]/1 mL; PENICILLIUM GLABRUM 5 [hp_X]/1 mL
INACTIVE INGREDIENTS: WATER

Pleo® Nota-Quent 5X

PURPOSE

Homeopathic Medicine

0.34 fl oz
(10 mL)

Indications

For temporary relief of bronchial and sinus congestion with fever and coughing due to colds and minor respiratory infections.

DOSAGE

5-10 drops, once daily, before mealtime.

WARNING

ASK DOCTOR

If symptoms persist more than a few days, contact a licensed practitioner.

PREGNANCY OR BREAST FEEDING

As with any drug, if you are pregnant or nursing a baby, seek the advice of a health care professional before using this product.

KEEP OUT OF REACH OF CHILDREN

Keep this and all other medications out of the reach of children. In case of accidental overdose, seek professional assistance or contact a Poison Control Center immediately. Protect from light and heat.

ACTIVE INGREDIENT

INGREDIENTS

10 mL contain 5 mL Penicillium chrysogenum 5X, 5 mL Penicillium glabrum 5X in a base of purified water.

Tamper Evident

Do not use this product if tamper-evident seal on base of bottle cap is missing or broken.

Manufactured by:
Sanum-Kehlbeck
GmbH & Co. KG
Hoya, Germany

Distributed by:
SANUM USA Corp.
1465 Slater Road
Ferndale, WA 98248

PRINCIPAL DISPLAY PANEL - 10 mL Bottle Carton

Pleo®
Nota-Quent

DROPS 5X
Homeopathic
Medicine

The original
SANUM®
brand remedies

Indications:
For temporary relief of
bronchial and
sinus congestion with
fever and coughing due
to colds and minor
respiratory infections.

ORIGINAL ENDERLEIN

0.34 fl oz
(10 mL)